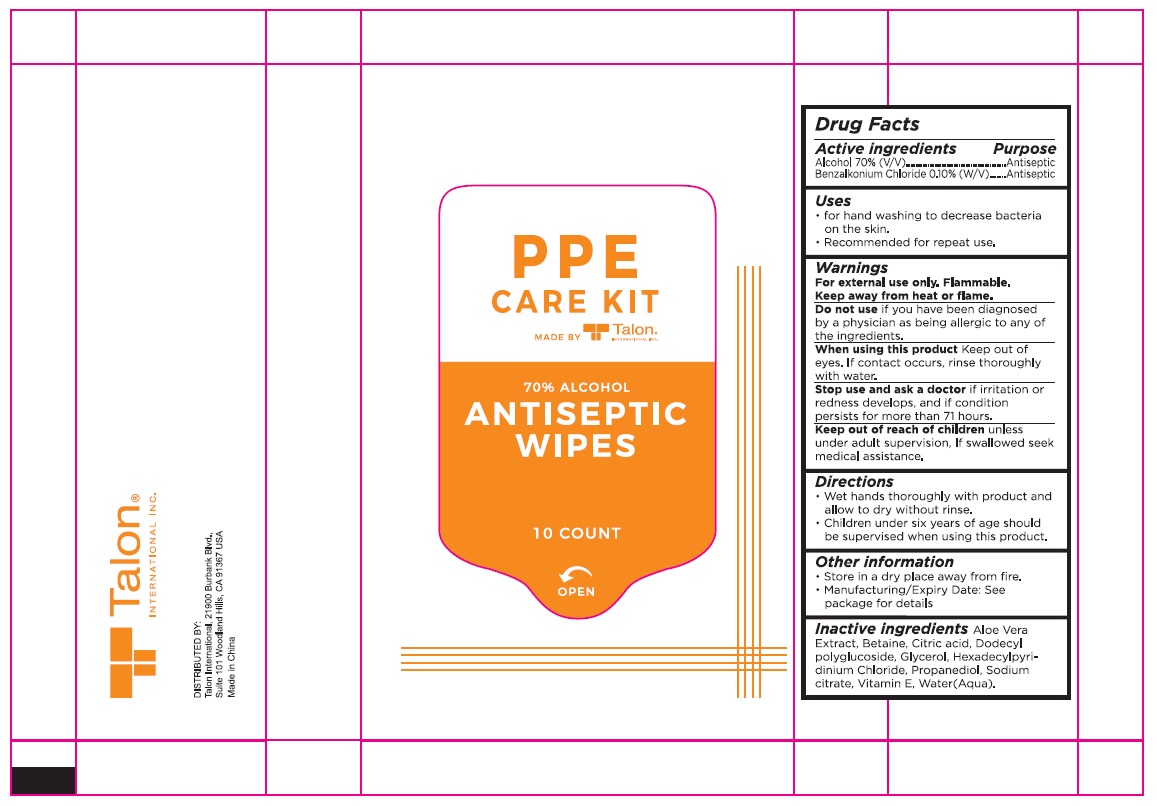 DRUG LABEL: Talon Antiseptic Wipes
NDC: 79891-003 | Form: CLOTH
Manufacturer: DOBOLV (QUANZHOU) PAPER CO., LTD
Category: otc | Type: HUMAN OTC DRUG LABEL
Date: 20201030

ACTIVE INGREDIENTS: ALCOHOL 70 mL/100 mL; BENZALKONIUM CHLORIDE 0.10 g/100 mL
INACTIVE INGREDIENTS: ALOE VERA LEAF; BETAINE; CITRIC ACID MONOHYDRATE; LAURYL GLUCOSIDE; GLYCERIN; CETYLPYRIDINIUM CHLORIDE ANHYDROUS; PROPANEDIOL; SODIUM CITRATE, UNSPECIFIED FORM; .ALPHA.-TOCOPHEROL; WATER

Talon® ANTISEPTIC WIPES

Active ingredients

Alcohol 70% (V/V)

Benzalkonium Chloride 0.10% (W/V)

Purpose

Antiseptic

Uses

• for hand washing to decrease bacteria on the skin.

• Recommended for repeat use.

Warnings

For external use only. Flammable.

Keep away from heat or flame.

Do not use if you have been diagnosed by a physician as being allergic to any of the ingredients.

When using this product Keep out of eyes. If contact occurs, rinse thoroughly with water.

Stop use and ask a doctor if irritation or redness develops, and if condition persists for more than 71 hours.

Keep out of reach of children unless under adult supervision, If swallowed seek medical assistance.

Directions

• Wet hands thoroughly with product and allow to dry without rinse.

• Children under six years of age should be supervised when using this product.

Other information

• Store in a dry place away from fire.

• Manufacturing/Expiry Date: See package for details

Inactive ingredients

Aloe Vera Extract, Betaine, Citric acid, Dodecyl polyglucoside, Glycerol, Hexadecylpyridinium Chloride, Propanediol, Sodium citrate, Vitamin E, Water(Aqua).

P P E CARE KIT

MADE BY Talon® INTERNATIONAL INC.

DISTRIBUTED BY:

Talon International, 21900 Burbank Blvd.,

Suite 101 Woodland Hills, CA 91367 USA

Made in China